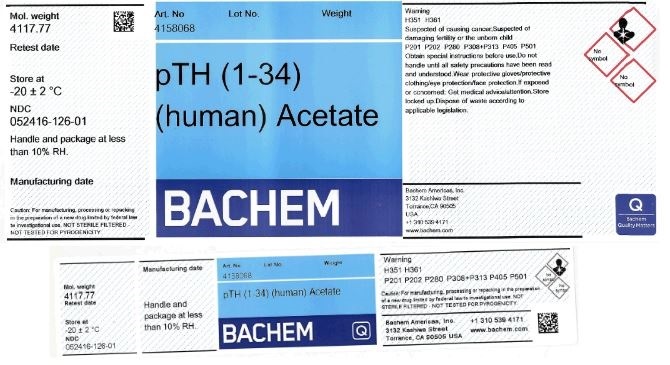 DRUG LABEL: Teriparatide Acetate (hPTH (1-34))
NDC: 52416-126 | Form: POWDER
Manufacturer: Bachem Americas, Inc.
Category: other | Type: BULK INGREDIENT
Date: 20240911

ACTIVE INGREDIENTS: TERIPARATIDE ACETATE 1 g/1 g

Product Listing for Teriparatide Acetate (hPTH(1-34))